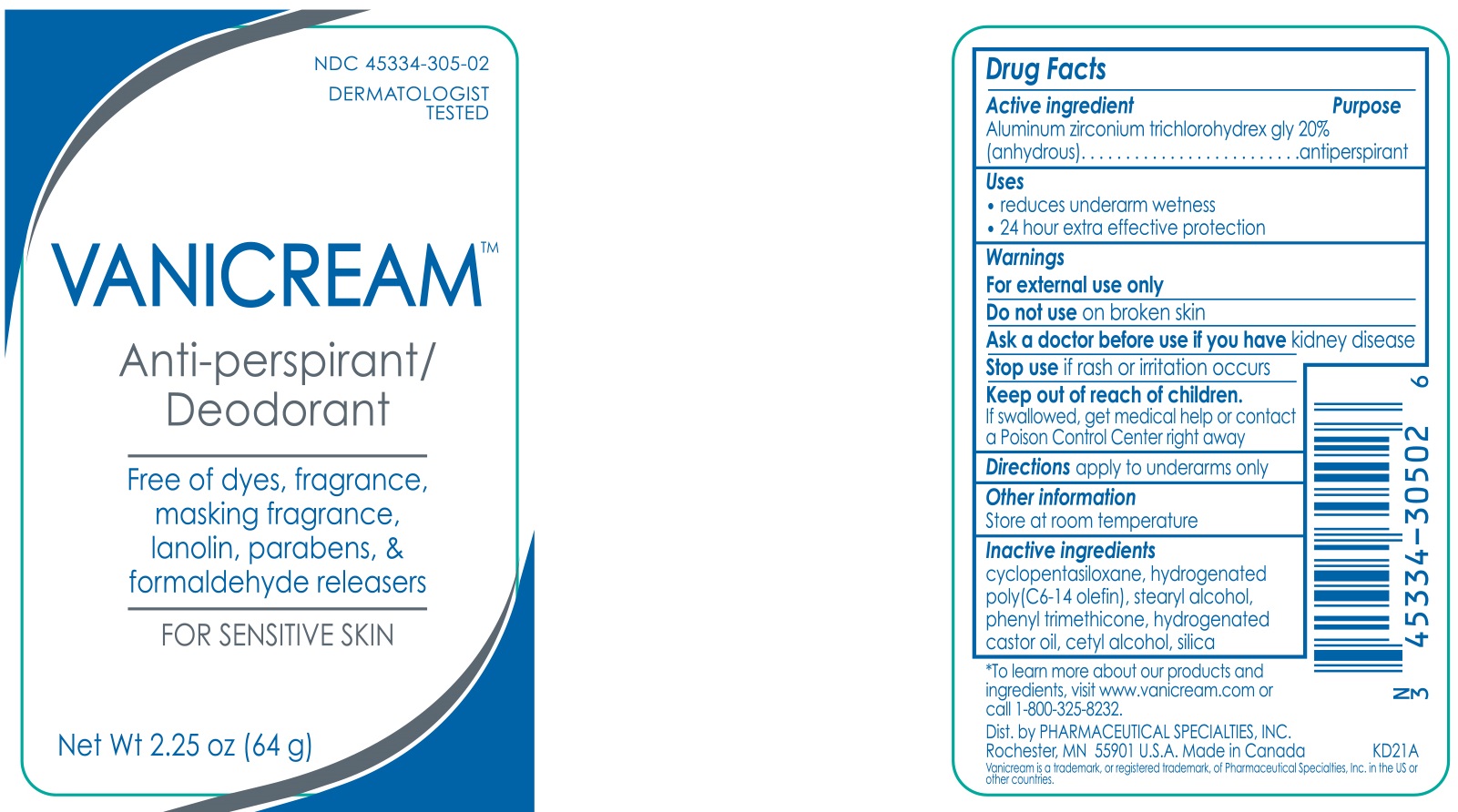 DRUG LABEL: Vanicream Anti-perspirant/Deodorant
NDC: 45334-305 | Form: STICK
Manufacturer: Pharmaceutical Specialties, Inc.
Category: otc | Type: HUMAN OTC DRUG LABEL
Date: 20231002

ACTIVE INGREDIENTS: ALUMINUM ZIRCONIUM TRICHLOROHYDREX GLY 12.8 g/64 g
INACTIVE INGREDIENTS: PHENYL TRIMETHICONE; HYDROGENATED CASTOR OIL; CETYL ALCOHOL; SILICON DIOXIDE; CYCLOMETHICONE 5; HYDROGENATED POLY(C6-14 OLEFIN; 6 CST); STEARYL ALCOHOL

VANICREAM Anti-perspirant/Deodorant

Active ingredient

Aluminum zirconium trichlorohydrex gly 20% (anhydrous)

Purpose

antiperspirant

Uses

- reduces underarm wetness
- 24 hour extra effective protection

Warnings

For external use only

Do not use on broken skin

Ask a doctor before use if you have kidney disease

Stop use if rash or irritation occurs

Keep out of reach of children. If swallowed, get medical help or contact a Poison Control Center right away

Directions

apply to underams only

Other information

Store at room temperature

Inactive ingredients

cyclopentasiloxane, hydrogenated poly(C6-14 olefin), stearyl alcohol, phenyl trimethicone, hydrogenated castor oil, cetyl alcohol, silica

*To learn more about our products and ingredients, visit www.vanicream.com or call 1-800-325-8232.

Dist. by PHARMACEUTICAL SPECIALTIES, INC.

Rochester, MN 55901 U.S.A.

Made in Canada

Vanicream is a trademark, or registered trademark, of Pharmaceutical Specialties, Inc. in the U.S. or other countries.

KD21A

PACKAGE LABEL

NDC 45334-305-02

DERMATOLOGIST TESTED

VANICREAM™

Anti-perspirant/Deodorant

Free of dyes, fragrance, masking fragrance, lanolin, parabens & formaldehyde releasers

FOR SENSITIVE SKIN

Net Wt 2.25 oz (64 g)